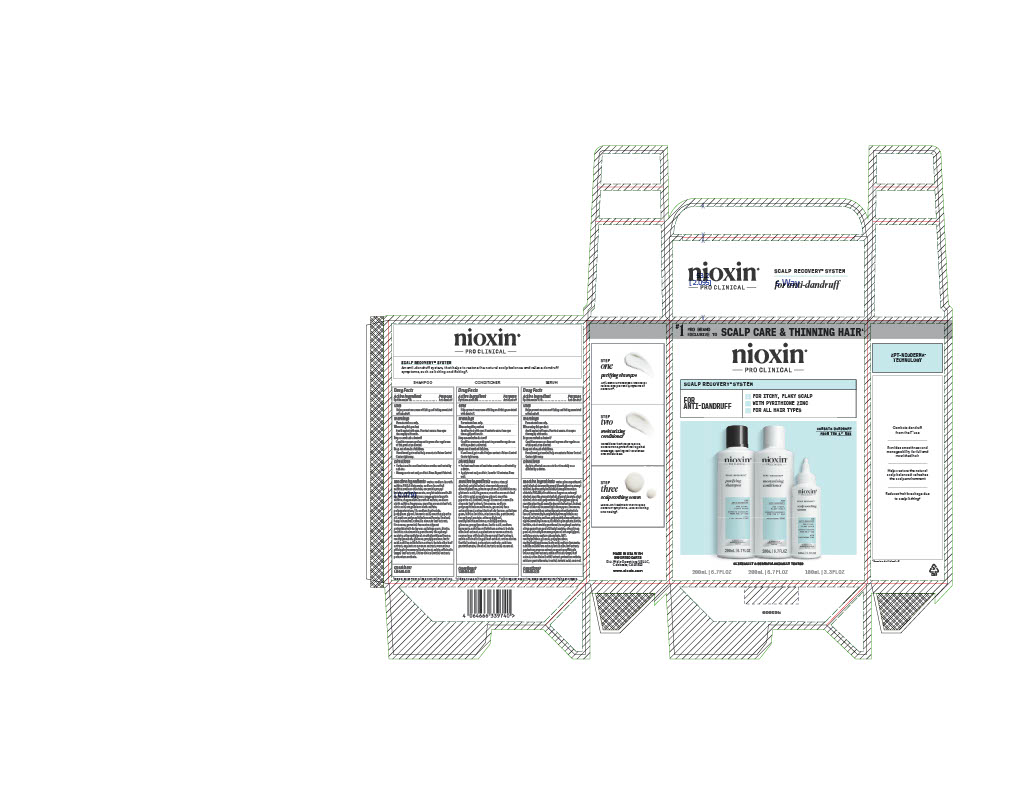 DRUG LABEL: nioxin PRO CLINICAL SCALP RECOVERY
NDC: 82157-014 | Form: KIT | Route: TOPICAL
Manufacturer: Wella Operations US LLC
Category: otc | Type: HUMAN OTC DRUG LABEL
Date: 20251125

ACTIVE INGREDIENTS: PYRITHIONE ZINC 0.5 g/100 mL; PYRITHIONE ZINC 1 g/100 mL; PYRITHIONE ZINC 0.1 g/100 mL
INACTIVE INGREDIENTS: INOSITOL; CELLULOSE GUM; DIMETHICONE; NIACINAMIDE; METHYLISOTHIAZOLINONE; CITRIC ACID; FORMALDEHYDE/SODIUM NAPHTHALENESULFONATE COPOLYMER (3000 MW); HEXYL CINNAMAL; GERANIOL; URTICA DIOICA LEAF; WATER; MENTHA ARVENSIS LEAF OIL; LECITHIN, SOYBEAN; ETHOXYDIGLYCOL; LACTIC ACID; PHENOXYETHANOL; SODIUM BENZOATE; EQUISETUM ARVENSE BRANCH; CARAMEL; ACHILLEA MILLEFOLIUM; YEAST, UNSPECIFIED; PANTHENOL; GLUCOSE; MENTHA PIPERITA (PEPPERMINT) OIL; PROPYLENE GLYCOL; SAGE; STEARYL ALCOHOL; POTASSIUM SORBATE; HEXAMETHYLINDANOPYRAN; BIOTIN; CETYL ALCOHOL; STEARAMIDOPROPYL DIMETHYLAMINE; GLUTAMIC ACID; .ALPHA.-TOCOPHEROL ACETATE, D-; LIMONENE, (+/-)-; ROSEMARY; BETULA ALBA LEAF; TARTARIC ACID; CALCIUM PANTOTHENATE; METHYLPARABEN; PROPYLPARABEN; LINALOOL, (+/-)-; CAMELLIA SINENSIS LEAF; WATER; ACHILLEA MILLEFOLIUM; FORMALDEHYDE/SODIUM NAPHTHALENESULFONATE COPOLYMER (3000 MW); LINALOOL, (+/-)-; HEXAMETHYLINDANOPYRAN; POTASSIUM SORBATE; CALCIUM PANTOTHENATE; SODIUM CHLORIDE; METHYLISOTHIAZOLINONE; CAMELLIA SINENSIS LEAF; TARTARIC ACID; SODIUM LAURETH SULFATE; PEG-3 DISTEARATE; ETHOXYDIGLYCOL; EQUISETUM ARVENSE BRANCH; SODIUM LAURETH-8 SULFATE; GERANIOL; BENZOIC ACID; GLUCOSE; .ALPHA.-TOCOPHEROL ACETATE, D-; POLYQUATERNIUM-10 (400 MPA.S AT 2%); LECITHIN, SOYBEAN; PROPYLPARABEN; SAGE; URTICA DIOICA LEAF; CELLULOSE GUM; NIACINAMIDE; INOSITOL; MAGNESIUM LAURETH SULFATE; PANTHENOL; ACRYLATES/STEARETH-20 METHACRYLATE COPOLYMER; PROPYLENE GLYCOL; LACTIC ACID; BETULA ALBA LEAF; CITRIC ACID; MENTHA PIPERITA (PEPPERMINT) OIL; SODIUM HYDROXIDE; METHYLPARABEN; BIOTIN; SODIUM OLETH SULFATE; MAGNESIUM LAURETH-8 SULFATE; LIMONENE, (+/-)-; MAGNESIUM OLETH SULFATE; YEAST, UNSPECIFIED; HEXYL CINNAMAL; ROSEMARY; MENTHA ARVENSIS LEAF OIL; COCAMIDOPROPYL BETAINE; CARAMEL; SODIUM BENZOATE; CETEARYL ALCOHOL; BIOTIN; TETRAMETHYL ACETYLOCTAHYDRONAPHTHALENES; LINALYL ACETATE; OLEYL ALCOHOL; LINALOOL, (+/-)-; ROSEMARY; MENTHA ARVENSIS LEAF OIL; PROPYLPARABEN; SODIUM BENZOATE; SAGE; GLYCERYL STEARATE; EQUISETUM ARVENSE BRANCH; PEG-2M; SODIUM PHOSPHATE; CETYL ALCOHOL; STEARAMIDOPROPYL DIMETHYLAMINE; DIMETHICONE; PROPYLENE GLYCOL; WATER; HYDROXYETHYLCELLULOSE; CITRUS AURANTIUM PEEL OIL; CITRUS LIMON (LEMON) PEEL OIL; ETHOXYDIGLYCOL; URTICA DIOICA LEAF; LACTIC ACID; CITRIC ACID; ACHILLEA MILLEFOLIUM; MENTHA PIPERITA (PEPPERMINT) OIL; STEARYL ALCOHOL; SILICA; DISTEARYLDIMONIUM CHLORIDE; .ALPHA.-TOCOPHEROL ACETATE, D-; PHENOXYETHANOL; PANTHENOL; INOSITOL; CARAMEL; METHYLISOTHIAZOLINONE; GERANIOL; DISODIUM PHOSPHATE; NIACINAMIDE; CELLULOSE GUM; TARTARIC ACID; HEXYL CINNAMAL; LECITHIN, SOYBEAN; POLYSORBATE 60; LIMONENE, (+/-)-; FORMALDEHYDE/SODIUM NAPHTHALENESULFONATE COPOLYMER (3000 MW); BETULA ALBA LEAF; TRIMETHYLBENZENEPROPANOL; BHT; BENZYL SALICYLATE; METHYLPARABEN; CALCIUM PANTOTHENATE; GLUCOSE; HEXAMETHYLINDANOPYRAN; ALPHA-ISOMETHYL IONONE; YEAST, UNSPECIFIED; POTASSIUM SORBATE; CAMELLIA SINENSIS LEAF

nioxin PRO CLINICAL SCALP RECOVERY SYSTEM FOR ANTI-DANDRUFF

Drug Facts

Active ingredient

Pyrithione zinc 1% (purifying shampoo)

Pyrithione zinc 0.5% (moisturizing conditioner)

Pyrithione zinc 0.1% (scalp soothing serum)

Purpose

Anti-dandruff

Uses

- Helps prevent recurrence of flaking and itching associated with dandruff.

Warnings
For external use only.

When using this product

- Avoid contact with eyes. If contact occurs, rinse eyes thoroughly with water.

Stop use and ask a doctor if

- Condition worsens or does not improve after regular use of this product as directed.

Keep out of reach of children. If swallowed, get medical help or contact a Poison Control Center right away.

Directions

PURIFYING SHAMPOO

- For best results use at least twice a week or as directed by a doctor.
- Massage on to wet scalp and hair. Rinse. Repeat if desired.

MOISTURIZING CONDITIONER

- For best results use at least twice a week or as directed by a doctor.
- Apply to wet scalp and hair, leave for 1-3 minutes. Rinse well.

SCALP SOOTHING SERUM

- Apply to affected areas one to four times daily or as directed by a doctor.

INACTIVE INGREDIENT

PURIFYING SHAMPOO

Inactive ingredients water, sodium laureth sulfate, PEG-3 distearate, sodium laureth-8 sulfate, sodium chloride, cocamidopropyl betaine, sodium benzoate, acrylates/steareth-20 methacrylate copolymer, magnesium laureth sulfate, magnesium laureth-8 sulfate, sodium oleth sulfate, fragrance, mentha arvensis leaf oil, citric acid, magnesium oleth sulfate, polyquaternium-10, sodium hydroxide, propylene glycol, benzoic acid, mentha piperita oil, sodium polynaphthalenesulfonate, linalool, hexyl cinnamal, camellia sinensis leaf extract, limonene, geraniol, faex extract/yeast extract/extrait de levure, cellulose gum, biotin, lecithin, niacinamide, panthenol, tocopheryl acetate, ethoxydiglycol, methylisothiazolinone, methylparaben, glucose, propylparaben, lactic acid, achillea millefolium extract, betula alba leaf extract, equisetum arvense extract, rosmarinus officinalis (rosemary) leaf extract, salvia officinalis (sage) leaf extract, urtica dioica (nettle) extract, potassium sorbate.

MOISTURIZING CONDITIONER

Inactive ingredients water, stearyl alcohol, cetyl alcohol, stearamidopropyl dimethylamine, phenoxyethanol, dimethicone, glutamic acid, fragrance, mentha arvensis leaf oil, citric acid, propylene glycol, mentha piperita oil, linalool, hexyl cinnamal, camellia sinensis leaf extract, limonene, sodium polynaphthalenesulfonate, geraniol, faex extract/yeast extract/extrait de levure, cellulose gum, biotin, lecithin, niacinamide, panthenol, tocopheryl acetate, ethoxydiglycol, methylisothiazolinone, methylparaben, glucose, propylparaben, lactic acid, sodium benzoate, achillea millefolium extract, betula alba leaf extract, equisetum arvense extract, rosmarinus officinalis (rosemary) leaf extract, salvia officinalis (sage) leaf extract, urtica dioica (nettle) extract, potassium sorbate, calcium pantothenate, inositol, tartaric acid, caramel.

SCALP SOOTHING SERUM

Inactive ingredients water, phenoxyethanol, cetyl alcohol, stearamidopropyl dimethylamine, stearyl alcohol, hydroxyethylcellulose, distearyldimonium chloride, PEG-2M, dimethicone, fragrance, cetearyl alcohol, mentha arvensis leaf oil, glyceryl stearate, oleyl alcohol, citric acid, polysorbate 60, propylene glycol, mentha piperita oil, camellia sinensis leaf extract, linalool, hexyl cinnamal, hexamethylindanopyran, limonene, silica, geraniol, faex extract/yeast extract/extrait de levure, tetramethyl acetyloctahydronaphthalenes, benzyl salicylate, sodium polynaphthalenesulfonate, alpha-isomethyl ionone, disodium phosphate, biotin, lecithin, niacinamide, panthenol, tocopheryl acetate, citrus aurantium peel oil, linalyl acetate, citrus limon peel oil, trimethylbenzenepropanol, ethoxydiglycol, cellulose gum, sodium phosphate, BHT, methylparaben, glucose, propylparaben, methylisothiazolinone, lactic acid, sodium benzoate, achillea millefolium extract, betula alba leaf extract, equisetum arvense extract, rosmarinus officinalis (rosemary) leaf extract, salvia officinalis (sage) leaf extract, urtica dioica (nettle) extract, potassium sorbate, calcium pantothenate, inositol, tartaric acid, caramel.

Questions?

1-800-935-5273

SCALP RECOVERY™ SYSTEM

An anti-dandruff system, that helps to restore the natural scalp balance and relieve dandruff symptoms, such as itching and flaking².

MADE IN USA WITH IMPORTED PARTS

Dist. Wella Operations US LLC,

Calabasas, CA 91302
www.nioxin.com

PACKAGE LABEL

nioxin® PRO CLINICAL

SCALP RECOVERY™ SYSTEM

FOR ANTI-DANDRUFF

FOR ITCHY, FLAKY SCALP

WITH PYRITHIONE ZINC

FOR ALL HAIR TYPES

CLINICALLY & DERMATOLOGICALLY TESTED

SCALP RECOVERY™; purifying shampoo | SCALP RECOVERY™; moisturizing conditioner | SCALP RECOVERY™; scalp soothing serum
200 mL | 6.7 FL OZ | 200 mL | 6.7 FL OZ | 100 mL | 3.3 FL OZ